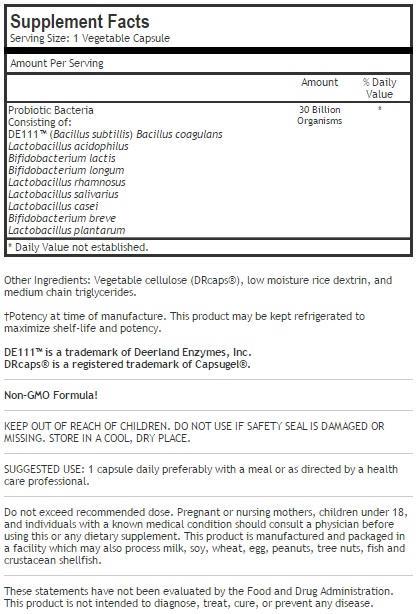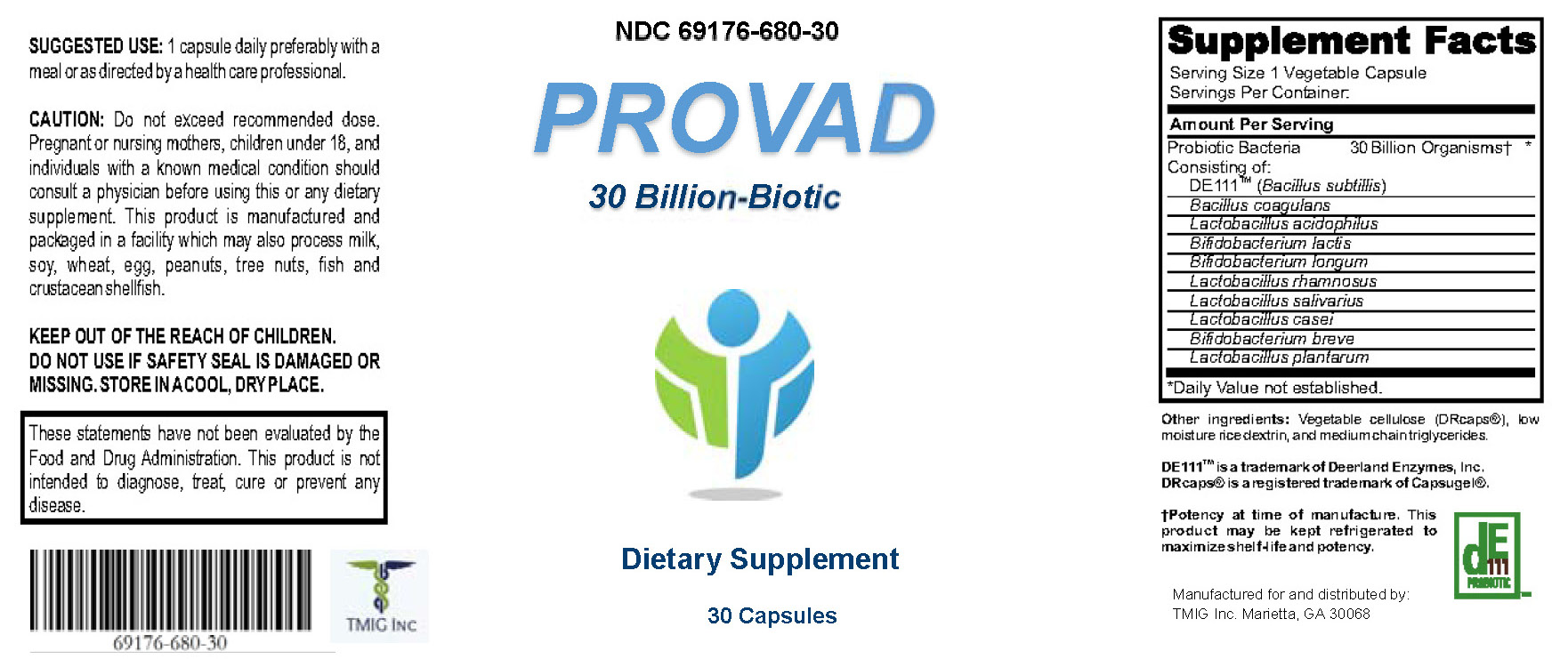 DRUG LABEL: Provad
NDC: 69176-680 | Form: CAPSULE
Manufacturer: TMIG Inc
Category: other | Type: DIETARY SUPPLEMENT
Date: 20190214

ACTIVE INGREDIENTS: BACILLUS SUBTILIS 26000000000 [CFU]/1 1; BACILLUS COAGULANS 1300000000 [CFU]/1 1; LACTOBACILLUS ACIDOPHILUS 250000000 [CFU]/1 1; BIFIDOBACTERIUM ANIMALIS LACTIS 250000000 [CFU]/1 1; BIFIDOBACTERIUM LONGUM 250000000 [CFU]/1 1; LACTOBACILLUS RHAMNOSUS 250000000 [CFU]/1 1; LACTOBACILLUS SALIVARIUS 250000000 [CFU]/1 1; LACTOBACILLUS CASEI 250000000 [CFU]/1 1; BIFIDOBACTERIUM BREVE 250000000 [CFU]/1 1; LACTOBACILLUS PLANTARUM 250000000 [CFU]/1 1

Prodvad Capsules
Dietary Supplement

DESCRIPTION

Provad is an orally administered prescription probiotic

Prodigen should be administered under the supervision of a licensed medical practitioner.

PLEASE NOTE: The product label name of "30 Billion-Biotic" is a descriptive marketing name only and not intended to represent the exact contents of the capsules. The actual product contains 29.3 Billion CFU. Please refer to details below for actual ingrediants and amounts.

WARNINGS AND PRECAUTIONS

This product is contraindicated in patients with a known hypersensitivity to any of the ingredients.

Provad should only be used under the direction and supervision of a licensed medical practitioner. Use with caution in patients that may have a medical condition, are pregnant, lactating, trying to conceive, under the age of 18, or taking medications.

DOSAGE AND ADMINISTRATION

Usual adult dose is 1 capsule daily with or without food or as prescribed by your doctor.

INDICATIONS AND USAGE

Provad is an orally administered prescription probiotic formulation for the clinical dietary management of suboptimal nutritional status in patients where advanced supplementation is required and nutritional supplementation in physiologically stressful conditions for maintenance of good health is needed.

HOW SUPPLIED:

Provad is supplied as apsules dispensed in 180cc plastic bottles of 30ct.

69176-680-30

Reserved for Professional Recommendation
All prescriptions using this product shall be pursuant to state statutes as applicable. This is not an Orange Book product. This product may be administered only under a physician’s supervision. There are no implied or explicit claims on therapeutic equivalence.
Manufactured for and distributed by:
TMIG INC, Marietta, GA 30062

STORAGE:

Store at controlled room temperature 15°-30°C (59°F-86°F). Keep in cool dry place. Call your doctor about side effects. You may report side effects to FDA at 1-800-FDA-1088.

KEEP THIS OUT OF THE REACH OF CHILDREN.

PACKAGE LABEL:

Rev2.1.19

Item 68030